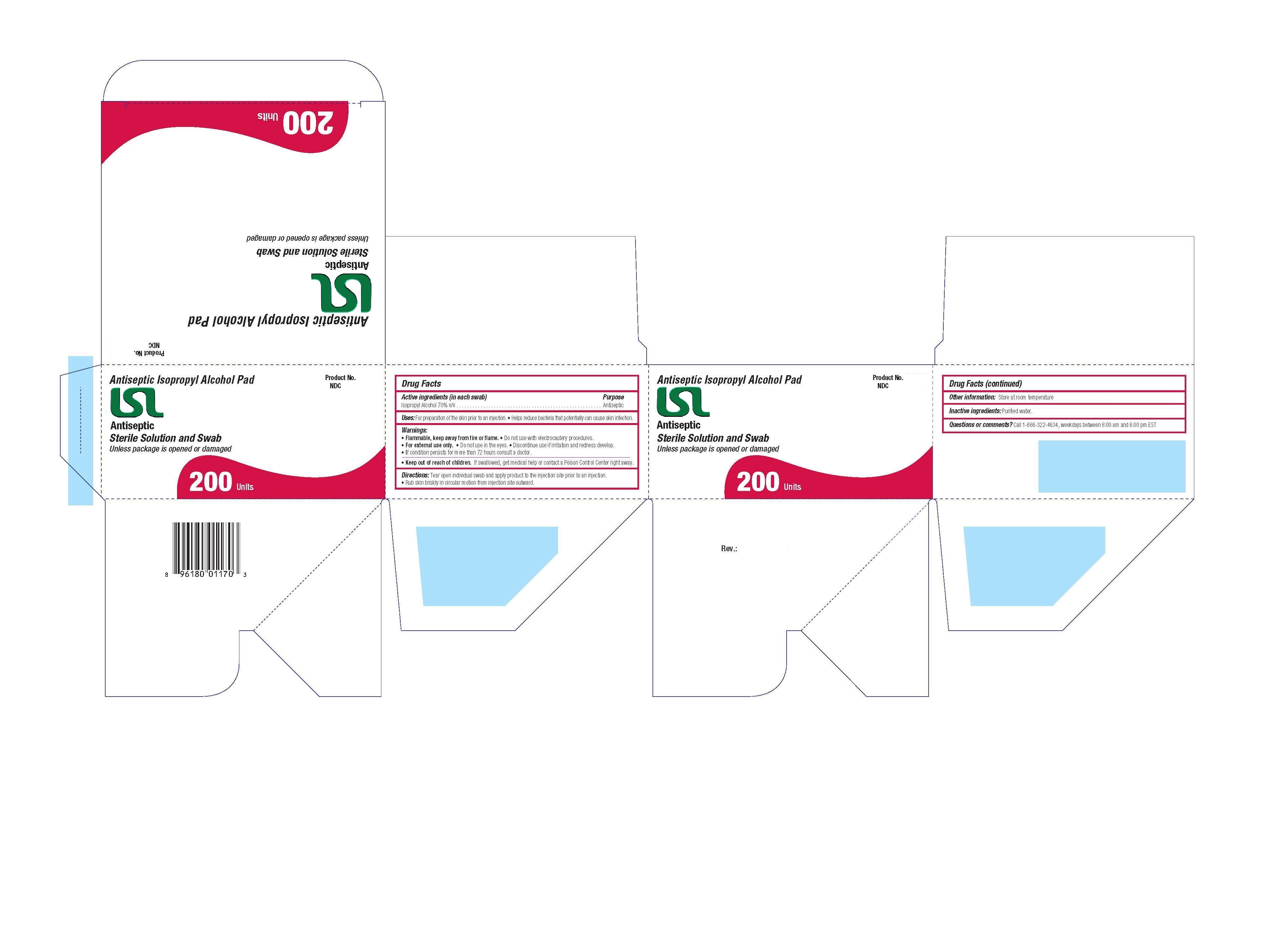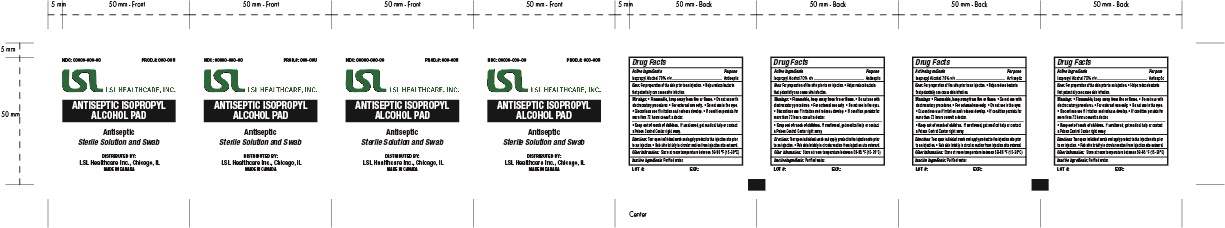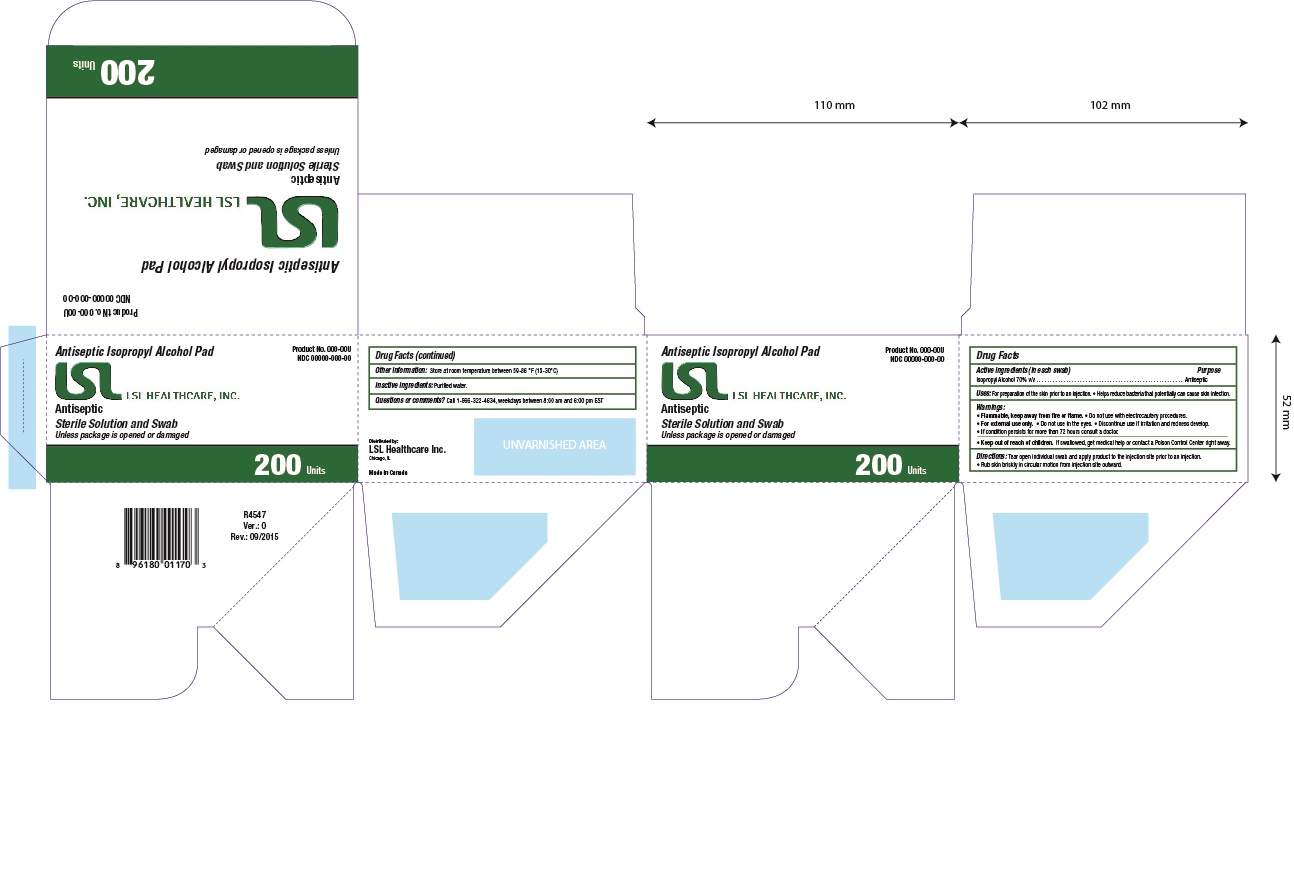 DRUG LABEL: ISOPROPYL ALCOHOL PREP PAD STERILE
NDC: 69789-104 | Form: SWAB
Manufacturer: LSL Industries Inc
Category: otc | Type: HUMAN OTC DRUG LABEL
Date: 20150514

ACTIVE INGREDIENTS: ISOPROPYL ALCOHOL 70 mL/100 mL
INACTIVE INGREDIENTS: WATER

Isopropyl Alcohol Prep Pad

Warnings

Flammable, keep away from fire or flame. Do not use with electrocautery procedures. For external use only. Do not use in the eyes. Discontinue use if irritation and redness develop. If condition persists for more than 72 hours consult a doctor Keep out of reach of children. If swallowed, get medical help or contact a Poison Control Center right away

Directions

Directions Tear open individual swab and apply product to the injection site prior to an injection.Rub skin briskly in circular motion from injection site outward

Purpose

Antiseptic

Keep out of reach of children

If swallowed, get medical help or contact a Poison Control Center right away.

Active Ingredient

Isopropyl Alcohol 70% v/v